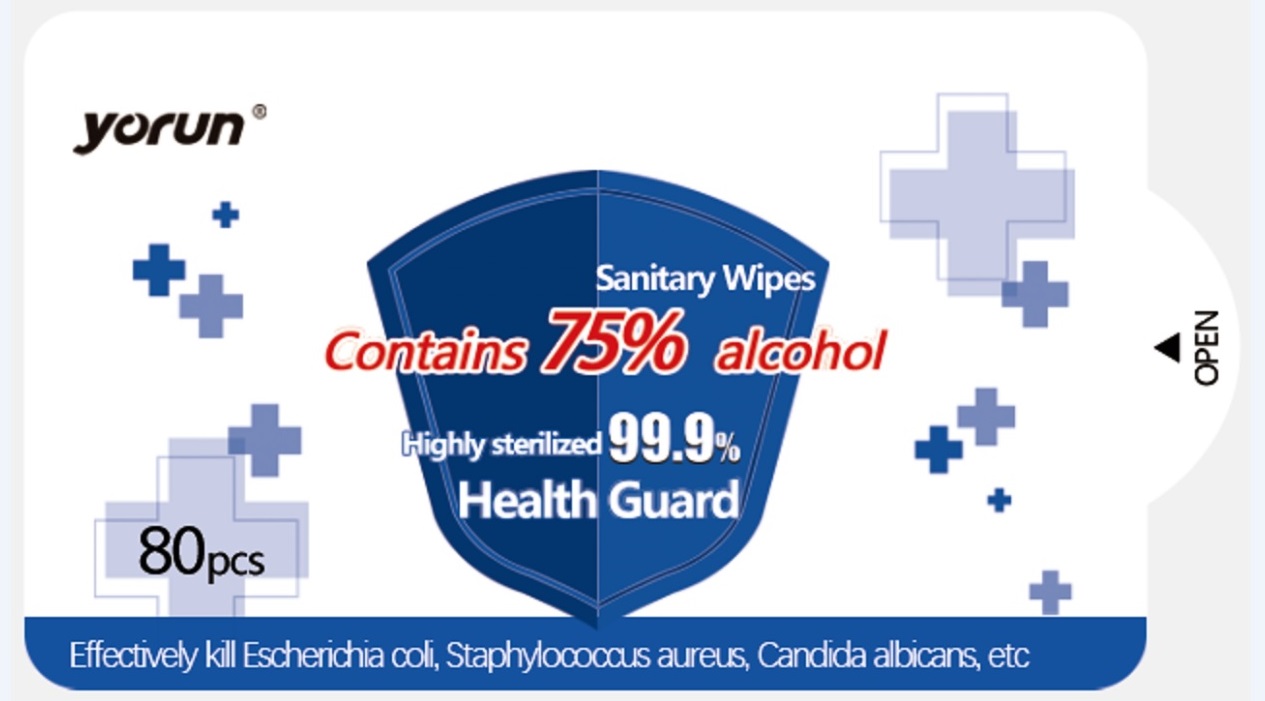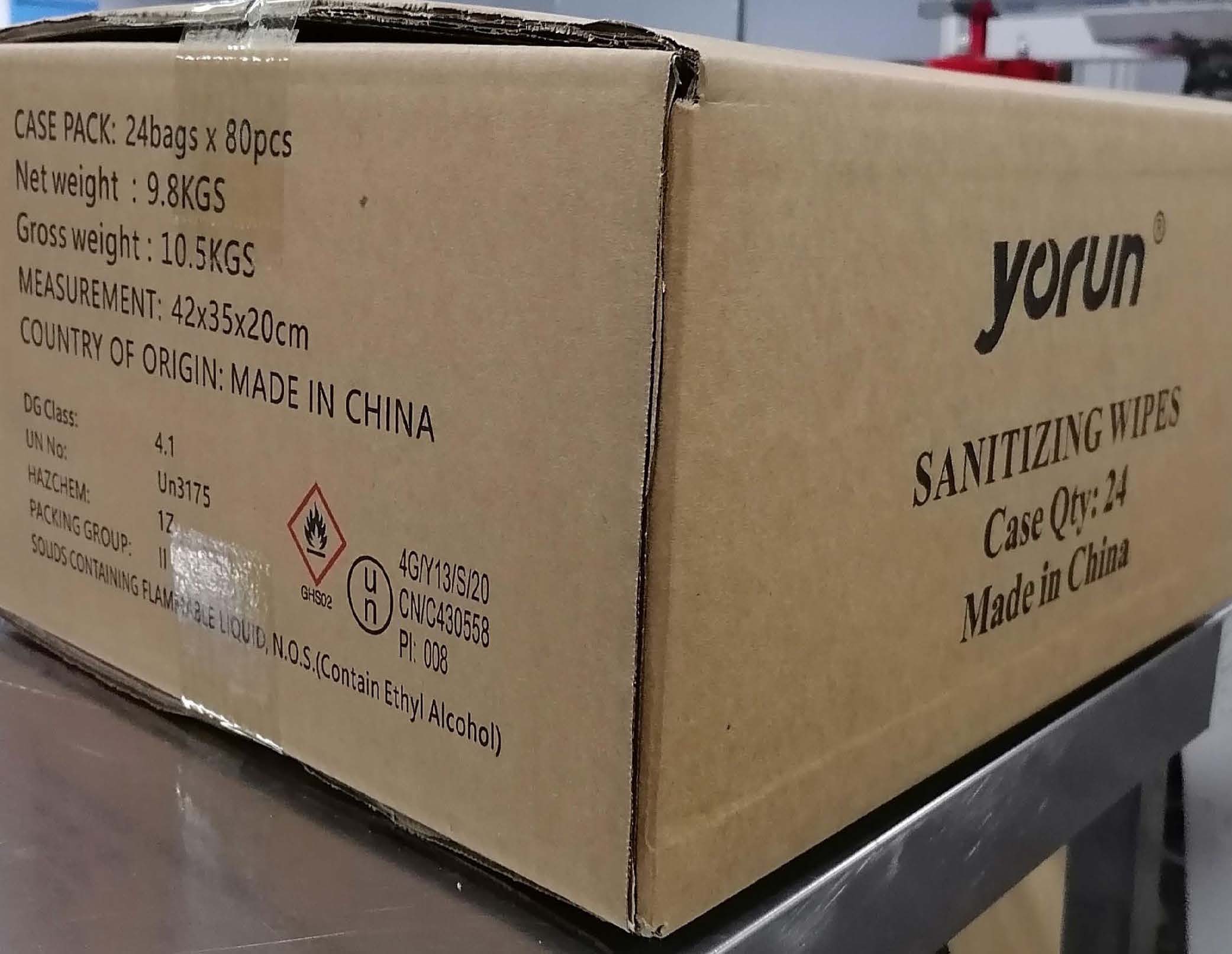 DRUG LABEL: YORUN Sanitizing Wipes
NDC: 75428-601 | Form: CLOTH
Manufacturer: Shandong BaiHe Sanitary Products Co., Ltd.
Category: otc | Type: HUMAN OTC DRUG LABEL
Date: 20200907

ACTIVE INGREDIENTS: ALCOHOL 75 1/100 1
INACTIVE INGREDIENTS: DIDECYLDIMONIUM CHLORIDE; WATER

YORUN Sanitizing Wipes

Active Ingredient(s)

Containing Alcohol 75%

Purpose

Purpose: Antibacterial Wipes

Use

YORUN Sanitizing Wipes effectively kill escherichia coli, staphylococcus aureus, candida albicans, etc.

Warnings

Flammable. For external use only. Keep away from heat or flame.

Do not use

- in children less than 2 months of age
- on open skin wounds

WHEN USING

In case of contact with eyes, rinse eyes thoroughly. Keep out with water if irritation or rash occurs. If swallowed, get medical help or contact a Poison Control Center right away

Stop use and ask a doctor if irritation or rash occurs.

Keep out of reach of children. If swallowed, get medical help or contact a Poison Control Center right away.

Directions

- Place enough product on hands to cover all surfaces. Rub hands together until dry. Supervise children under 6 years of age when using this product to avoid swallowing.

Other information

- Dispose of wipe in trash after each use. Avoid freezing and excessive heat above 40℃(104F).

Inactive ingredients

PURE WATER, DOUBLE-CHAIN QUATERNARY AMMONIUM SALT